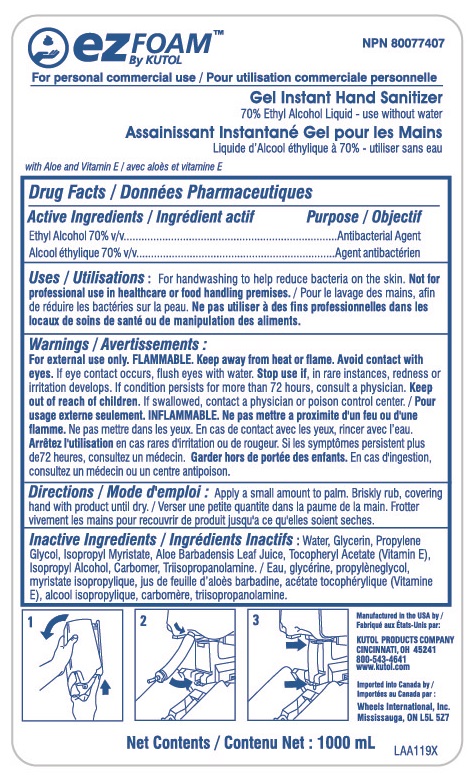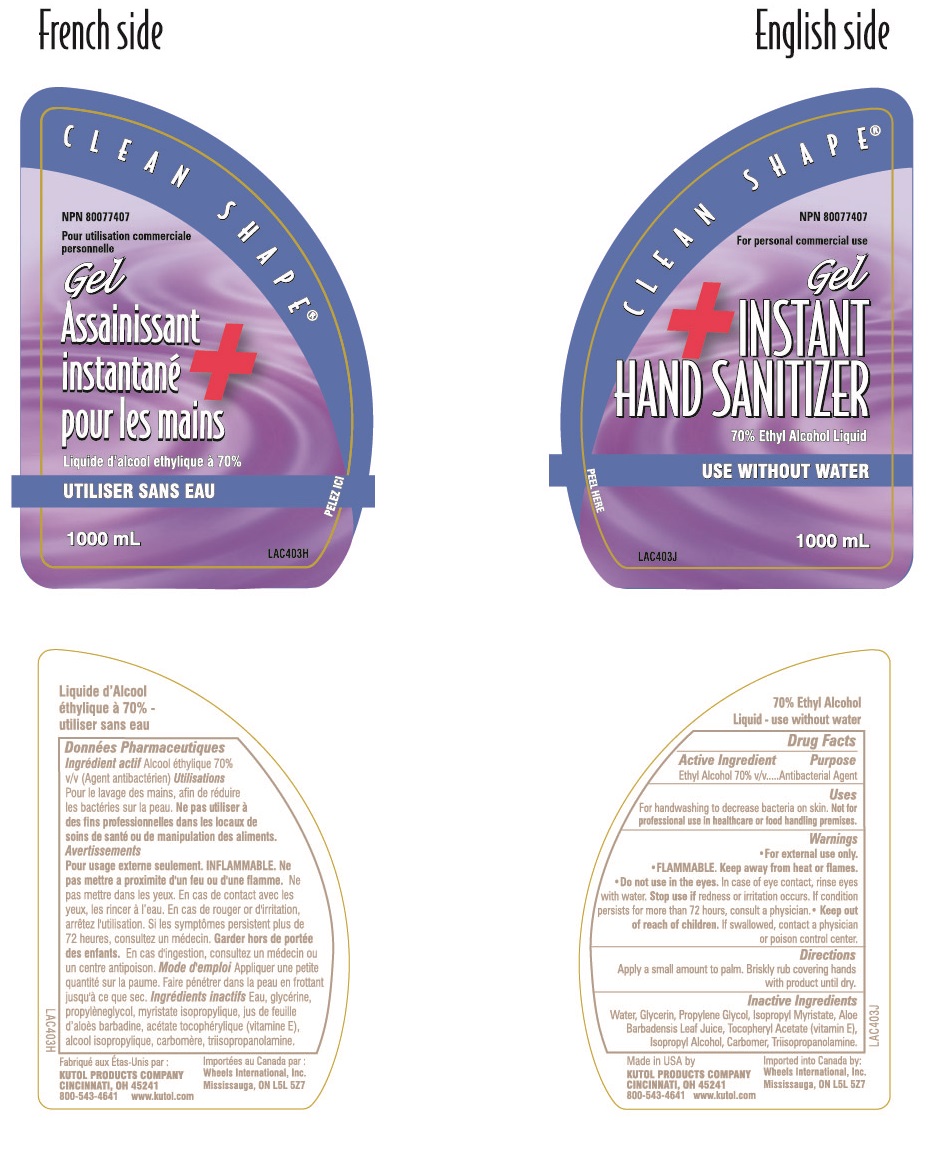 DRUG LABEL: Gel Instant Hand Sanitizer
NDC: 50865-370 | Form: SOAP
Manufacturer: Kutol Products
Category: otc | Type: HUMAN OTC DRUG LABEL
Date: 20190116

ACTIVE INGREDIENTS: ALCOHOL 0.07 mg/1 mL
INACTIVE INGREDIENTS: PROPYLENE GLYCOL; GLYCERIN; ISOPROPYL ALCOHOL; .ALPHA.-TOCOPHEROL ACETATE, D-; TRIISOPROPANOLAMINE; ALOE VERA LEAF; ISOPROPYL MYRISTATE; WATER; CARBOXYPOLYMETHYLENE

Active Ingredients / Ingrédient actif

Ethyl Alcohol 70% v/v

Alcool éthylique 70% v/v

Purpose / Objectif

Antibacterial Agent

Agent antibactérien

INDICATIONS AND USAGE

Uses / Utilisations: For handwashing to help reduce bacteria on the skin. Not for professional use in healthcare or food handling premises. / Pour le lavage des mains, afin de réduire les bactéries sur la peau. Ne pas utiliser à des fins professionelles dans les locaux de soins de santé ou de manipulation des aliments.

Keep out of reach of children.

Garder hors de portée des enfants.

Warnings / Avertissements :

For external use only. FLAMMABLE. Keep away from heat or flame. Avoid contact with eyes. If eye contact occurs, flush eyes with water. Stop use if, in rare instances, redness or irritation develops. If condition persists for more than 72 hours, consult a physician. /

Pour usage externe seulement. INFLAMMABLE. Ne pas mettre a proximite d'un feu ou d'une flamme. Ne pas mettre dans les yeux. En cas de contact avec les yeux, rincer avec l'eau. Arrêtex l'utilisation en cas rares d'irritation ou de rougeru. Si les symptômes persistent plus de 72 heures, consultez en médecin. Garder hors de portée des enfants. En cas d'ingestion, consultez un médecin ou un centre antipoison.

DOSAGE AND ADMINISTRATION

Directions / Mode d'emploi : Apply a small amount to palm. Briskly rub, covering hand with product until dry. / Verser une petite quantite dans la paume de la main. Frotter vivement les mains pour recouvrir de produit jusqu'a ce qu'elles soient seches.

INACTIVE INGREDIENT

Inactive Ingredients / Ingrédients Inactifs : water, glycerin, propylene glycol, ispropyl myristate, aloe barbadensis leaf juice, tocopheryl acetate (Vitamin E), isopropyl alcohol, carbomer, triisopropanolamine. / Eau, glycérine, propylèneglycol, myristate isopropylique, jus de feuille d'aloès barbadine, acétate tocophérylique (Vitamine E), alcool isopropylique, carbomère, triisopropanolamine.